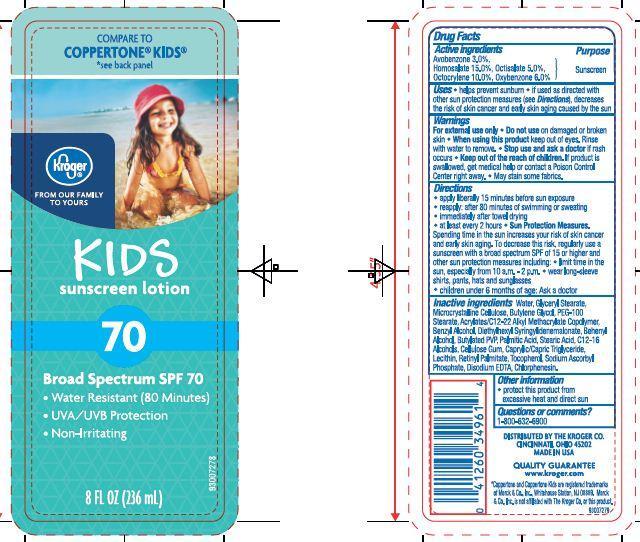 DRUG LABEL: Kroger Kids Sunscreen
NDC: 30142-927 | Form: LOTION
Manufacturer: THE KROGER CO
Category: otc | Type: HUMAN OTC DRUG LABEL
Date: 20130911

ACTIVE INGREDIENTS: AVOBENZONE 3 g/100 g; HOMOSALATE 15 g/100 g; OCTISALATE 5 g/100 g; OCTOCRYLENE 10 g/100 g; OXYBENZONE 6 g/100 g
INACTIVE INGREDIENTS: WATER; DOCOSANOL; PALMITIC ACID; PEG-100 STEARATE; GLYCERYL MONOSTEARATE; STEARIC ACID; EDETATE DISODIUM; LAURYL ALCOHOL; MYRISTYL ALCOHOL; CHLORPHENESIN; CETYL ALCOHOL; CELLULOSE, MICROCRYSTALLINE; CARBOXYMETHYLCELLULOSE SODIUM; BUTYLENE GLYCOL; DIETHYLHEXYL SYRINGYLIDENEMALONATE; TRICAPRIN; BENZYL ALCOHOL; TOCOPHEROL; VITAMIN A PALMITATE; SODIUM ASCORBYL PHOSPHATE

Drug Facts

Active ingredients

Avobenzone 3.0 %

Homosalate 15.0%

Octisalate 5.0%

Octocrylene 10.0%

Oxybenzone 6.0%

Purpose

Sunscreen

Uses

- Helps prevent sunburn
- If used as directed with other sun protection measures (see Directions), decrease the risk of skin cancer and early skin aging caused by the sun

Warnings

For external use only. Do not use on damaged or broken skin.

When using this product

- keep out of eyes. Rinse with water to remove.

Stop use and ask a doctor if

- rash occurs

Keep out of reach of children.

If swallowed, get medical help or contact a Poison Control Center right away.

Directions

- apply liberally 15 minutes before sun exposure
- reapply
- after 80 minutes of swimming or sweating
- immediately after towel drying
- at least every 2 hours
- Sun Protection Measures: Spending time in the sun increases your risk of skin cancer and early skin aging. To decrease this risk, regularly use a sunscreen with a broad spectrum SPF of 15 or higher and other sun protection measures including:
- limit time in the sun, especially from 10 a.m. - 2 p.m.
- wear long-sleeve shirts, pants, hats and sunglasses
- children under 6 months of age: Ask a doctor

Other information

- protect this product from excessive heat and direct sun

Inactive ingredients

Water, Glyceryl Stearate, Microcrystalline Cellulose, Butylene Glycol, PEG-100 Stearate, Acrylates/C12-22 Alkyl Methacrylate Copolymer, Benzyl Alcohol, Diethylhexyl Syringylidenemalonate, Behenyl Alcohol, Butylated PVP, Palmitic Acid, Stearic Acid, C12-16 Alcohols, Cellulose Gum, Caprylic/Capric Triglyceride, Lecithin, Retinyl Palmitate, Tocopherol, Sodium Ascorbyl Phosphate, Disodium EDTA, Chlorphenesin.

Principal Display Panel

COMPARE TO COPPERTONE KIDS

see back panel

Kroger

FROM OUR FAMILY TO YOURS

KIDS

sunscreen lotion

70

Broad Spectrum SPF 70

Water Resistant (80 Minutes)

UVA/UVB Protection

Non-Irritating

8 Fl OZ (236 mL)

Questions or comments?

1-800-632-6900